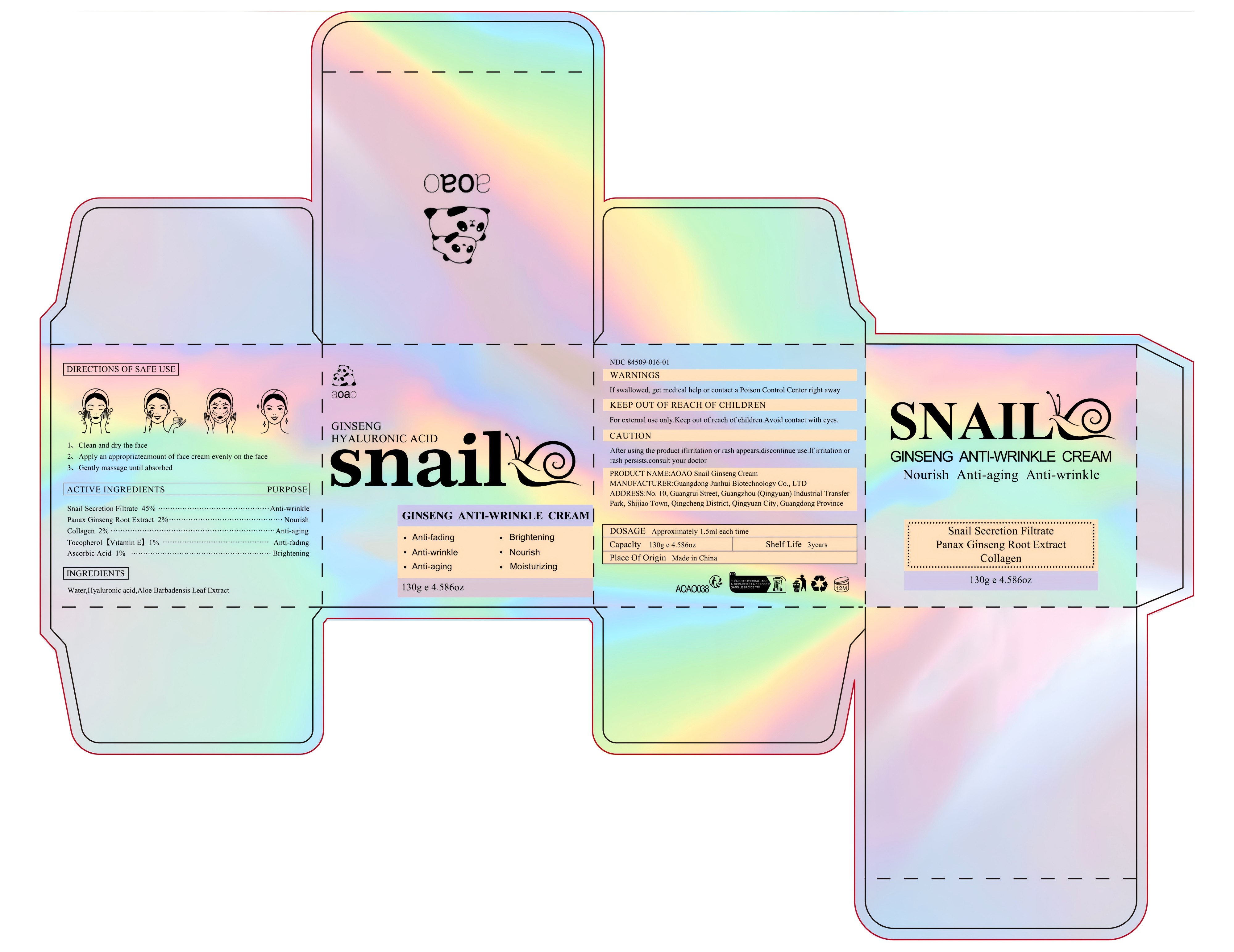 DRUG LABEL: AOA0 Snail Ginseng Cream
NDC: 84509-016 | Form: CREAM
Manufacturer: Guangdong Junhui Biotechnology Co., LTD
Category: otc | Type: HUMAN OTC DRUG LABEL
Date: 20250108

ACTIVE INGREDIENTS: GARDEN SNAIL MUCIN 58500 mg/130 g; ASIAN GINSENG 2600 mg/130 g; COLLAGEN, SOLUBLE, FISH SKIN 2600 mg/130 g; TOCOPHEROL 1300 mg/130 g; ASCORBIC ACID 1300 mg/130 g
INACTIVE INGREDIENTS: WATER; HYALURONIC ACID; ALOE VERA LEAF

Active Ingredients

Snail Secretion Filtrate 45%
Panax Ginseng Root Extract 2%
Collagen 2%
Tocopherol 1%
Ascorbic Acid 1%

Purpose

Anti-wrinkle
Nourish
Anti-aging
Anti-fading
Brightening

Uses

1、 Clean and dry the face
2、 Apply an appropriateamount of face cream evenly on the face
3、Gently massage until absorbed

Inactive Ingredients

AOA0 Snail & Ginseng Cream

Warnings

For external use only. Keep out ofreach of children.Avoid contact with eyes

Keep out of reach of children

If swallowed, get medical help or contact a Poison Control Center right away

CAUTION

After using the product ifirritation or rash appears,discontinue use.Ifirritation or
rash persists.consult your doctor.

DOSAGE

Approximately 1.5ml each time

Inactive Ingredients

Water,Hyaluronic acid,Aloe Barbadensis Leaf Extract.

Manufacturer

Guangdong Junhui Biotechnology Co., LTD

ADDRESS

No. 10, Guangrui Street, Guangzhou (Qingyuan) Industrial Transfer Park, Shijiao Town, Qingcheng District, Qingyuan City, Guangdong Province

Capacity

130g e 4.5860z

Shelf Life

3 Years

Place of Origin

Made in China